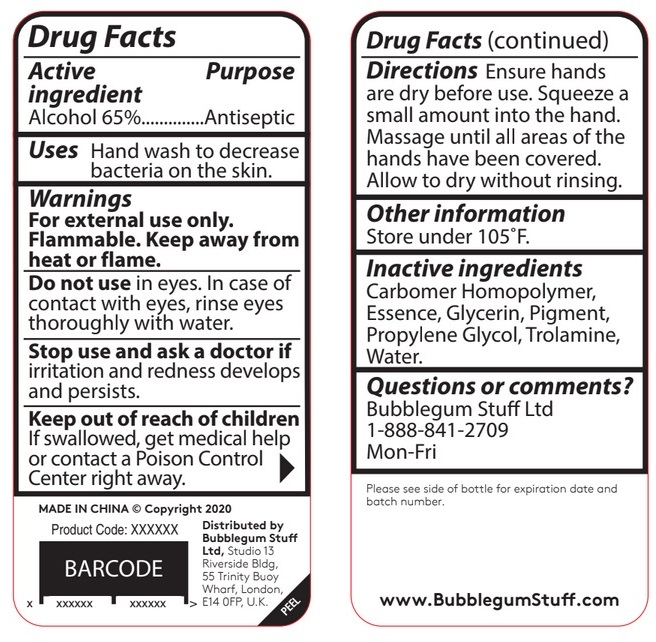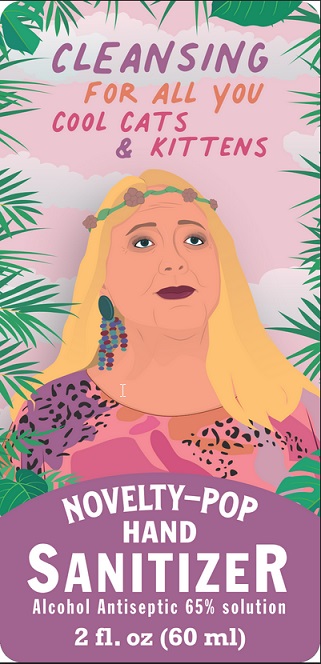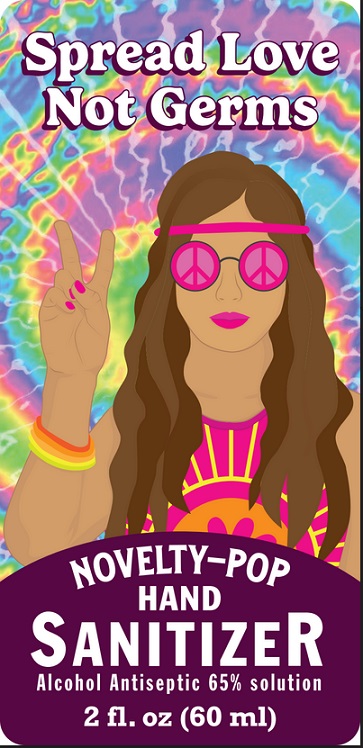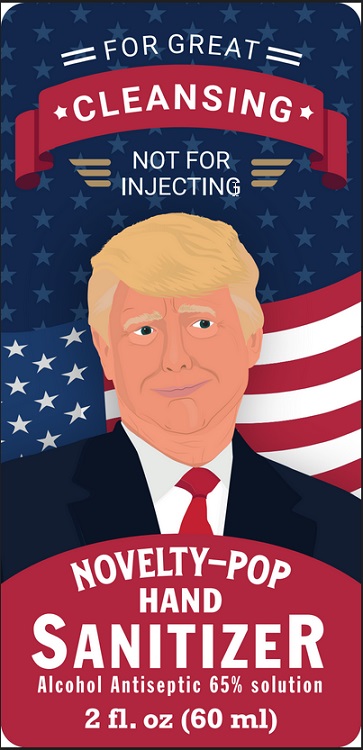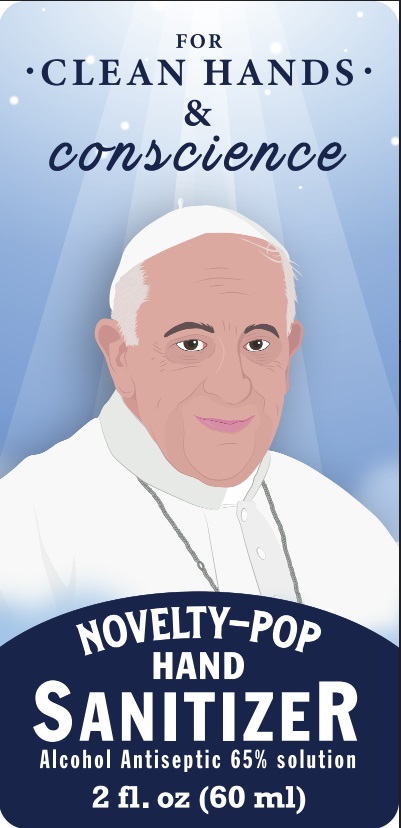 DRUG LABEL: Novelty-Pop Hand Sanitizer
NDC: 80257-001 | Form: GEL
Manufacturer: BUBBLEGUM STUFF LTD
Category: otc | Type: HUMAN OTC DRUG LABEL
Date: 20200909

ACTIVE INGREDIENTS: ALCOHOL 65 mL/100 mL
INACTIVE INGREDIENTS: WATER; GLYCERIN; PROPYLENE GLYCOL; CARBOMER HOMOPOLYMER, UNSPECIFIED TYPE; TROLAMINE

Active Ingredient

Alcohol 65% v/v.

Purpose

Antiseptic

Use

Hand wash to decrease bacteria on the skin.

Warnings

For external use only.

Flammable. Keep away from heat or flame.

Do not use in eyes. In case of contact with eyes, rinse eyes thoroughly with water.
Stop use and ask a doctor if irritation and redness develops and persists.

Keep out of reach of children. If swallowed, get medical help or contact a Poison Control Center right away.

Directions

Ensure hands are dry before use. Squeeze a small amount into the hand. Massage until all areas of the hands have been covered. Allow to dry without rinsing.

Other information

Store under 105°F.

Inactive ingredients

Carbomer Homopolymer, Essence, Glycerin, Pigment, Propylene Glycol, Trolamine, Water.

Questions or comments?
Bubblegum Stuff Ltd
1-888-841-2709
Mon-Fri